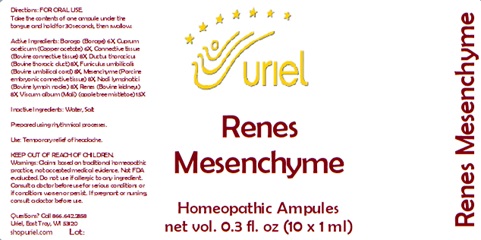 DRUG LABEL: Renes Mesenchyme
NDC: 48951-8130 | Form: LIQUID
Manufacturer: Uriel Pharmacy Inc.
Category: homeopathic | Type: HUMAN OTC DRUG LABEL
Date: 20241212

ACTIVE INGREDIENTS: BOS TAURUS LYMPH VESSEL 8 [hp_X]/1 mL; BOS TAURUS CARTILAGE 8 [hp_X]/1 mL; PORK KIDNEY 8 [hp_X]/1 mL; VISCUM ALBUM FRUITING TOP 15 [hp_X]/1 mL; CUPRIC ACETATE 6 [hp_X]/1 mL; BORAGE 6 [hp_X]/1 mL; BOS TAURUS CONJUNCTIVA 8 [hp_X]/1 mL; SUS SCROFA UMBILICAL CORD 8 [hp_X]/1 mL
INACTIVE INGREDIENTS: WATER; SODIUM CHLORIDE

Renes Mesenchyme

INDICATIONS AND USAGE

Directions: FOR ORAL USE ONLY.

DOSAGE AND ADMINISTRATION

Take the contents of one ampule under the tongue and hold for 30 seconds, then swallow.

ACTIVE INGREDIENT

Active Ingredients: Borago (Borage) 6X, Cuprum aceticum (Copper acetate) 6X, Connective tissue (Bovine connective tissue) 8X, Ductus thoracicus (Bovine thoracic duct) 8X, Funiculus umbilicalis (Bovine umbilical cord) 8X, Mesenchyme (Porcine embryonic connective tissue) 8X, Nodi lymphatici (Bovine lymph nodes) 8X, Renes (Bovine kidneys) 8X, Viscum Mali (Apple tree mistletoe) 15X

Inactive Ingredients: Water, Salt

Prepared using rhythmical processes.

PURPOSE

Use: Temporary relief of headache.

KEEP OUT OF REACH OF CHILDREN.

WARNINGS

Warnings: Claims based on traditional homeopathic practice, not accepted medical evidence. Not FDA evaluated. Do not use if allergic to any ingredient. Consult a doctor before use for serious conditions or if conditions worsen or persist. If pregnant or nursing, consult a doctor before use.

QUESTIONS

Questions? Call 866.642.2858 Uriel, East Troy, WI 53120 shopuriel.com Lot: